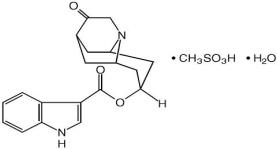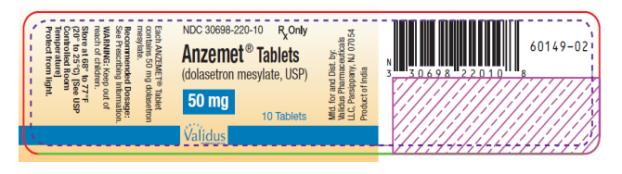 DRUG LABEL: ANZEMET
NDC: 30698-220 | Form: TABLET, FILM COATED
Manufacturer: Validus Pharmaceuticals LLC
Category: prescription | Type: HUMAN PRESCRIPTION DRUG LABEL
Date: 20231212

ACTIVE INGREDIENTS: DOLASETRON MESYLATE 50 mg/1 1
INACTIVE INGREDIENTS: CROSCARMELLOSE SODIUM; HYPROMELLOSES; LACTOSE, UNSPECIFIED FORM; MAGNESIUM STEARATE; POLYETHYLENE GLYCOL, UNSPECIFIED; POLYSORBATE 80; STARCH, CORN; FERRIC OXIDE RED; TITANIUM DIOXIDE

Anzemet

ANZEMET ® Tablets
(dolasetron mesylate, USP)

Rx Only

DESCRIPTION

ANZEMET (dolasetron mesylate, USP) is an antinauseant and antiemetic agent. Chemically, dolasetron mesylate is (2α,6α,8α,9aß)-octahydro-3-oxo-2,6-methano-2H-quinolizin-8-yl-1H-indole-3-carboxylate monomethanesulfonate, monohydrate. It is a highly specific and selective serotonin subtype 3 (5-HT3) receptor antagonist both in vitro and in vivo. Dolasetron mesylate has the following structural formula:

The empirical formula is C19H20N2O3 • CH3SO3H • H2O, with a molecular weight of 438.50. Approximately 74% of dolasetron mesylate monohydrate is dolasetron base.

Dolasetron mesylate monohydrate is a white to off-white powder that is freely soluble in water and propylene glycol, slightly soluble in ethanol, and slightly soluble in normal saline.

Each ANZEMET Tablet for oral administration contains dolasetron mesylate (as the monohydrate) and also contains the inactive ingredients: croscarmellose sodium, hypromellose, lactose, magnesium stearate, polyethylene glycol, polysorbate 80, pregelatinized starch, synthetic red iron oxide, and titanium dioxide.

CLINICAL PHARMACOLOGY

Dolasetron mesylate and its active metabolite, hydrodolasetron (MDL 74,156), are selective serotonin 5-HT3 receptor antagonists not shown to have activity at other known serotonin receptors and with low affinity for dopamine receptors. The serotonin 5-HT3 receptors are located on the nerve terminals of the vagus in the periphery and centrally in the chemoreceptor trigger zone of the area postrema. It is thought that chemotherapeutic agents produce nausea and vomiting by releasing serotonin from the enterochromaffin cells of the small intestine, and that the released serotonin then activates 5-HT3 receptors located on vagal efferents to initiate the vomiting reflex.

In healthy volunteers (N=64), dolasetron mesylate in single intravenous doses up to 5 mg/kg produced no effect on pupil size or meaningful changes in EEG tracings. Results from neuropsychiatric tests revealed that dolasetron mesylate did not alter mood or concentration. Multiple daily doses of dolasetron have had no effect on colonic transit in humans. Dolasetron has no effect on plasma prolactin concentrations.

Effects on Electrocardiogram

QTcF interval was evaluated in a randomized, placebo and active (moxifloxacin 400 mg once-daily) controlled crossover study in 80 healthy adults, with 14 measurements over 24 hours on Day 4. The maximum mean (95% upper confidence bound) differences in QTcF from placebo after baseline-correction were 14.1 (16.1) ms and 36.6 (38.6) ms for 100 mg and supratherapeutic 300 mg ANZEMET, administered intravenously, respectively. ANZEMET 300 mg once daily resulted in approximately 3-fold higher mean Cmax values of dolasetron mesylate and its active metabolite hydrodolasetron on Day 4 compared to those observed with the therapeutic 100 mg ANZEMET dose.

Based on exposure-response analysis in healthy volunteers, QTc interval prolongations appear to be associated with concentrations of hydrodolasetron. Using the established exposure-response relationship, the mean predicted increase (95% upper prediction interval) in QTcF intervals were 16.0 (17.1) ms and 17.9 (19.1) ms for renally impaired and elderly subjects following an oral dose of 100 mg.

In the thorough QT study, exposure dependent prolongation of the PR and QRS interval was also noted in healthy subjects receiving ANZEMET. The maximum mean (95% upper confidence bound) difference in PR from placebo after baseline-correction was 9.8 (11.6) ms and 33.1 (34.9) ms for 100 mg and supratherapeutic 300 mg ANZEMET, respectively. The maximum mean (95% upper confidence bound) difference in QRS from placebo after baseline-correction was 3.5 (4.5) ms and 13 (14.5) ms for 100 mg and supratherapeutic 300 mg ANZEMET, respectively. Over one-fourth of the subjects treated with the 300 mg dose had an absolute PR over 200 ms and absolute QRS of over 110 ms post-treatment. A change from baseline ≥ 25% was noted in several of these subjects (see WARNINGS).

Pharmacokinetics in Humans

Oral dolasetron is well absorbed, although parent drug is rarely detected in plasma due to rapid and complete metabolism to the most clinically relevant species, hydrodolasetron.

The reduction of dolasetron to hydrodolasetron is mediated by a ubiquitous enzyme, carbonyl reductase. Cytochrome P-450 (CYP) 2D6 is primarily responsible for the subsequent hydroxylation of hydrodolasetron and both CYP3A and flavin monooxygenase are responsible for the N-oxidation of hydrodolasetron.

Hydrodolasetron is excreted in the urine unchanged (61.0% of administered oral dose). Other urinary metabolites include hydroxylated glucuronides and N-oxide.

Hydrodolasetron appears rapidly in plasma, with a maximum concentration occurring approximately 1 hour after dosing, and is eliminated with a mean half-life of 8.1 hours (%CV=18%) and an apparent clearance of 13.4 mL/min/kg (%CV=29%) in 30 adults. The apparent absolute bioavailability of oral dolasetron, determined by the major active metabolite hydrodolasetron, is approximately 75%. Orally administered dolasetron intravenous solution and tablets are bioequivalent. Food does not affect the bioavailability of dolasetron taken by mouth.

Hydrodolasetron is eliminated by multiple routes, including renal excretion and, after metabolism, mainly, glucuronidation and hydroxylation. Two thirds of the administered dose is recovered in the urine and one third in the feces. Hydrodolasetron is widely distributed in the body with a mean apparent volume of distribution of 5.8 L/kg (%CV=25%, N=24) in adults.

Sixty-nine to 77% of hydrodolasetron is bound to plasma protein. In a study with ^14C labeled dolasetron, the distribution of radioactivity to blood cells was not extensive. Approximately 50% of hydrodolasetron is bound to α1-acid glycoprotein. The pharmacokinetics of hydrodolasetron are linear and similar in men and women.

The pharmacokinetics of hydrodolasetron, in special and targeted patient populations following oral administration of dolasetron, are summarized in Table 1. The pharmacokinetics of hydrodolasetron are similar in adult (young and elderly) healthy volunteers and in adult cancer patients receiving chemotherapeutic agents. The apparent clearance following oral administration of hydrodolasetron is approximately 1.6- to 3.4-fold higher in children and adolescents than in adults. The clearance following oral administration of hydrodolasetron is not affected by age in adult cancer patients. The apparent oral clearance of hydrodolasetron decreases 42% with severe hepatic impairment and 44% with severe renal impairment. No dose adjustment is necessary for renally impaired or elderly patients, however ECG monitoring is recommended (see WARNINGS and PRECAUTIONS, Geriatric Use). No dose adjustment is recommended for patients with hepatic impairment.

The pharmacokinetics of ANZEMET Tablets have not been studied in the pediatric population. However, the following pharmacokinetic data are available on intravenous ANZEMET Injection administered orally to children.

Thirty-two pediatric cancer patients ages 3 to 11 years (N=19) and 12 to 17 years (N=13), received 0.6, 1.2, or 1.8 mg/kg ANZEMET Injection diluted with either apple or apple-grape juice and administered orally. In this study, the mean apparent clearances of hydrodolasetron were 3 times greater in the younger pediatric group and 1.8 times greater in the older pediatric group than those observed in healthy adult volunteers. Across this spectrum of pediatric patients, maximum plasma concentrations were 0.6 to 0.7 times those observed in healthy adults receiving similar doses.

For 12 pediatric patients, ages 2 to 12 years receiving 1.2 mg/kg ANZEMET Injection diluted in apple or apple-grape juice and administered orally, the mean apparent clearance was 34% greater and half-life was 21% shorter than in healthy adults receiving the same dose.

The table below summarizes the pharmacokinetic data from multiple populations. Please note that the doses studied may have exceeded the maximum recommended dose.

Table 1. Pharmacokinetic Values for Plasma Hydrodolasetron Following Oral Administration of ANZEMET*
 | Age (years) | Dose | CLapp (mL/min/kg) | t 1/2 (h) | Cmax (ng/mL)
Young Healthy Volunteers (N=30) | 19-45 | 200 mg | 13.4 (29%) | 8.1 (18%) | 556 (28%)
Elderly Healthy Volunteers (N=15) | 65-75 | 2.4 mg/kg | 9.5 (36%) | 7.2 (32%) | 662 (28%)
Cancer Patients Adults (N=61) † Adolescents (N=13) Children (N=19) | 24-84 12-17 3-11 | 25-200 mg 0.6-1.8 mg/kg 0.6-1.8 mg/kg | 12.9 (49%) 26.5 (67%) 44.2 (49%) | 7.9 (43%) 6.4 (30%) 5.5 (39%) | --‡ 374§ (32%) 217|| (67%)
Patients with Severe Renal Impairment (N=12) (Creatinine clearance ≤10 mL/min) | 28-74 | 200 mg | 7.2 (48%) | 10.7 (29%) | 701 (21%)
Patients with Severe Hepatic Impairment (N=3) | 42-52 | 150 mg | 8.8 (57%) | 11.0 (36%) | 410 (12%)
CLapp: apparent clearance
t1/2: terminal elimination half-life
(): coefficient of variation in %
*: mean values
†: analyzed by nonlinear mixed effect modeling with data pooled across dose strengths
‡: sampling times did not allow calculation
§: results from adolescents (dose=1.8 mg/kg, N=3) the maximum dose exceeded 100 mg. When data from patients who received greater than 47 mg (N=9) are combined and normalized to the 1.8 mg/kg dose with a cap of 100 mg, the mean Cmax was 229 ng/mL (51%).
| |: results from children (dose=1.8 mg/kg, N=7)

Clinical Studies

Oral ANZEMET at a dose of 100 mg prevents nausea and vomiting associated with moderately emetogenic cancer therapy as shown by 24 hour efficacy data from two double-blind studies. Efficacy was based on complete response (i.e., no vomiting, no rescue medication).

The first randomized, double-blind trial compared single oral ANZEMET doses of 25, 50, 100 and 200 mg in 60 men and 259 women cancer patients receiving cyclophosphamide and/or doxorubicin. There was no statistically significant difference in complete response between the 100 mg and 200 mg dose. Results are summarized in Table 2.

Table 2. Prevention of Chemotherapy-Induced Nausea and Vomiting from Moderately Emetogenic Chemotherapy
 | ANZEMET Tablets
Response Over 24 Hours | 25 mg (N=78) | 50 mg (N=83) | 100 mg† (N=80) | 200 mg (N=78) | p-value for Linear Trend
Complete Response‡ | 24 (31%) | 34 (41%) | 49 (61%) | 46 (59%) | P<.0001
Nausea Score§ | 49 | 10 | 11 | 7 | P=.0006
†: The recommended dose
‡: No emetic episodes and no rescue medication.
§: Median 24-h change from baseline nausea score using visual analog scale (VAS): Score range 0= “none” to 100= “nausea as bad as it could be.”

Another trial also compared single oral ANZEMET doses of 25, 50, 100, and 200 mg in 307 patients receiving moderately emetogenic chemotherapy. In this study, the 100 mg ANZEMET dose gave a 73% complete response rate.

INDICATIONS AND USAGE

ANZEMET Tablets are indicated for the prevention of nausea and vomiting associated with moderately emetogenic cancer chemotherapy, including initial and repeat courses in adults and children 2 years and older.

CONTRAINDICATIONS

ANZEMET Tablets are contraindicated in patients known to have hypersensitivity to the drug.

WARNINGS

QT Interval Prolongation

ANZEMET prolongs the QT interval in a dose dependent fashion. Torsade de Pointes has been reported during post-marketing experience. Avoid ANZEMET in patients with congenital long QT syndrome, hypomagnesemia, or hypokalemia. Hypokalemia and hypomagnesemia must be corrected prior to ANZEMET administration. Monitor these electrolytes after administration as clinically indicated. Use ECG monitoring in patients with congestive heart failure, bradycardia, renal impairment, and elderly patients (see CLINICAL PHARMACOLOGY).

PR and QRS Interval Prolongation

ANZEMET has been shown to cause dose dependent prolongation of the PR and QRS interval and reports of second or third degree atrioventricular block, cardiac arrest and serious ventricular arrhythmias including fatalities in both adult and pediatric patients. At particular risk are patients with underlying structural heart disease and preexisting conduction system abnormalities, elderly, patients with sick sinus syndrome, patients with atrial fibrillation with slow ventricular response, patients with myocardial ischemia or patients receiving drugs known to prolong the PR interval (such as verapamil) and QRS interval (e.g., flecainide or quinidine). ANZEMET should be used with caution and with ECG monitoring in these patients. ANZEMET should be avoided in patients with complete heart block or at risk for complete heart block, unless they have an implanted pacemaker (see CLINICAL PHARMACOLOGY).

Serotonin Syndrome

The development of serotonin syndrome has been reported with 5-HT3 receptor antagonists. Most reports have been associated with concomitant use of serotonergic drugs (e.g., selective serotonin re-uptake inhibitors (SSRIs), serotonin and norepinephrine re-uptake inhibitors (SNRIs), monoamine oxidase inhibitors, mirtazapine, fentanyl, lithium, tramadol, and intravenous methylene blue). Some of the reported cases were fatal. Serotonin syndrome occurring with overdose of another 5-HT3 receptor antagonist alone has also been reported. The majority of reports of serotonin syndrome related to 5-HT3 receptor antagonist use occurred in a post-anesthesia care unit or an infusion center.

Symptoms associated with serotonin syndrome may include the following combination of signs and symptoms: mental status changes (e.g., agitation, hallucinations, delirium, and coma), autonomic instability (e.g., tachycardia, labile blood pressure, dizziness, diaphoresis, flushing, hyperthermia), neuromuscular symptoms (e.g., tremor, rigidity, myoclonus, hyperreflexia, incoordination), seizures, with or without gastrointestinal symptoms (e.g., nausea, vomiting, diarrhea). Patients should be monitored for the emergence of serotonin syndrome, especially with concomitant use of Anzemet and other serotonergic drugs. If symptoms of serotonin syndrome occur, discontinue Anzemet and initiate supportive treatment. Patients should be informed of the increased risk of serotonin syndrome, especially if Anzemet is used concomitantly with other serotonergic drugs (see DRUG INTERACTIONS, Patient Counseling Information).

PRECAUTIONS

General

Dolasetron should be administered with caution in patients who have or may develop prolongation of cardiac conduction intervals, particularly QTc. These include patients with hypokalemia or hypomagnesemia, patients taking diuretics with potential for inducing electrolyte abnormalities, patients with congenital QT syndrome, patients taking anti-arrhythmic drugs or other drugs which lead to QT prolongation, and cumulative high dose anthracycline therapy.

Cross hypersensitivity reactions have been reported in patients who received other selective 5-HT3 receptor antagonists. These reactions have not been seen with dolasetron mesylate.

Drug Interactions

The potential for clinically significant drug-drug interactions posed by dolasetron and hydrodolasetron appears to be low for drugs commonly used in chemotherapy because hydrodolasetron is eliminated by multiple routes. See PRECAUTIONS, General for information about potential interaction with other drugs that prolong the QTc interval.

When oral dolasetron (200 mg once daily) was co-administered with cimetidine (300 mg four times daily) for 7 days, the systemic exposure (i.e., AUC) of hydrodolasetron increased by 24% and the maximum plasma concentration of hydrodolasetron increased by 15%. When oral dolasetron (200 mg once daily) was co-administered with rifampin (600 mg once daily) for 7 days, the systemic exposure of hydrodolasetron decreased by 28% and the maximum plasma concentration of hydrodolasetron decreased by 17%.

Caution should be exercised when ANZEMET is co-administered with drugs, including those used in chemotherapy, that prolong ECG intervals and/or cause hypokalemia or hypomagnesemia (see WARNINGS).

In patients taking furosemide, nifedipine, diltiazem, ACE inhibitors, verapamil, glyburide, propranolol, and various chemotherapy agents, no effect was shown on the clearance of hydrodolasetron. Clearance of hydrodolasetron decreased by about 27% when dolasetron mesylate was administered intravenously concomitantly with atenolol. Dolasetron mesylate did not inhibit the antitumor activity of four chemotherapeutic agents (cisplatin, 5-fluorouracil, doxorubicin, cyclophosphamide) in four murine models.

Serotonin syndrome (including altered mental status, autonomic instability, and neuromuscular symptoms) has been described following the concomitant use of 5-HT3 receptor antagonists and other serotonergic drugs, including selective serotonin re-uptake inhibitors (SSRIs) and serotonin and noradrenaline re-uptake inhibitors (SNRIs).

Carcinogenesis, Mutagenesis, Impairment of Fertility

In a 24-month carcinogenicity study, there was a statistically significant (P<0.001) increase in the incidence of combined hepatocellular adenomas and carcinomas in male mice treated with 150 mg/kg/day and above. In this study, mice (CD-1) were treated orally with dolasetron mesylate 75, 150, or 300 mg/kg/day (225, 450 or 900 mg/m^2/day). For a 50 kg person of average height (1.46 m^2 body surface area), these doses represent 3, 6, and 12 times the recommended clinical dose (74 mg/m^2) on a body surface area basis. No increase in liver tumors was observed at a dose of 75 mg/kg/day in male mice and at doses up to 300 mg/kg/day in female mice.

In a 24-month rat (Sprague-Dawley) carcinogenicity study, oral dolasetron mesylate was not tumorigenic at doses up to 150 mg/kg/day (900 mg/m^2/day, 12 times the recommended human dose based on body surface area) in male rats and 300 mg/kg/day (1800 mg/m^2/day, 24 times the recommended human dose based on body surface area) in female rats.

Dolasetron mesylate was not genotoxic in the Ames test, the rat lymphocyte chromosomal aberration test, the Chinese hamster ovary (CHO) cell (HGPRT) forward mutation test, the rat hepatocyte unscheduled DNA synthesis (UDS) test or the mouse micronucleus test.

Dolasetron mesylate was found to have no effect on fertility and reproductive performance at oral doses up to 100 mg/kg/day (600 mg/m^2/day, 8 times the recommended human dose based on body surface area) in female rats and up to 400 mg/kg/day (2400 mg/m^2/day, 32 times the recommended human dose based on body surface area) in male rats.

Pregnancy: Teratogenic Effects.

Teratology studies have not revealed evidence of impaired fertility or harm to the fetus due to dolasetron mesylate. These studies have been performed in pregnant rats at oral doses up to 100 mg/kg/day (8 times the recommended human dose based on body surface area) and pregnant rabbits at oral doses up to 100 mg/kg/day (16 times the recommended human dose based on body surface area). There are, however, no adequate and well-controlled studies in pregnant women. Because animal reproduction studies are not always predictive of human response, this drug should be used during pregnancy only if clearly needed.

Nursing Mothers

It is not known whether dolasetron mesylate is excreted in human milk. Because many drugs are excreted in human milk, caution should be exercised when ANZEMET Tablets are administered to a nursing woman.

Pediatric Use (see PRECAUTIONS, General)

Safety and effectiveness in pediatric patients (2 years and older) is based on pharmacokinetic studies and efficacy data in adults. Safety and effectiveness in pediatric patients under 2 years of age have not been established.

ANZEMET Tablets are expected to be as safe and effective as when ANZEMET Injection is given orally to pediatric patients. ANZEMET Tablets are recommended for children old enough to swallow tablets (see CLINICAL PHARMACOLOGY, Pharmacokinetics in Humans).

Geriatric Use

Elderly patients are at particular risk for prolongation of the PR, QRS, and QT interval; therefore, caution should be exercised and ECG monitoring should be performed when using ANZEMET in this population (see WARNINGS).

In controlled clinical trials in the prevention of chemotherapy-induced nausea and vomiting, 301 (29%) of 1026 patients were 65 years of age or older. Of the 301 geriatric patients in the trial, 282 received oral ANZEMET Tablets. No overall differences in safety or effectiveness were observed between geriatric and younger patients, and other reported clinical experience has not identified differences in responses between geriatric and younger patients, but greater sensitivity of some older individuals cannot be ruled out.

The pharmacokinetics, including clearance of oral ANZEMET Tablets, in elderly and younger patients are similar (see CLINICAL PHARMACOLOGY, Pharmacokinetics in Humans). Dosage adjustment is not needed in patients over the age of 65.

ADVERSE REACTIONS

In controlled clinical trials, 943 adult cancer patients received ANZEMET Tablets. These patients were receiving concurrent chemotherapy, predominantly cyclophosphamide and doxorubicin regimens. The following adverse events were reported in ≥2% of patients receiving either ANZEMET 25 mg or ANZEMET 100 mg tablets for prevention of cancer chemotherapy induced nausea and vomiting in controlled clinical trials (Table 3).

Table 3. Adverse Events ≥2% from Chemotherapy-Induced Nausea and Vomiting Studies
 | ANZEMET
Event | 25 mg (N=235) | 100 mg (N=227)
Headache | 42 (17.9%) | 52 (22.9%)
Fatigue | 6 (2.6%) | 13 (5.7%)
Diarrhea | 5 (2.1%) | 12 (5.3%)
Bradycardia | 12 (5.1%) | 9 (4.0%)
Dizziness | 3 (1.3%) | 7 (3.1%)
Pain | 0 | 7 (3.1%)
Tachycardia | 7 (3.0%) | 6 (2.6%)
Dyspepsia | 7 (3.0%) | 5 (2.2%)
Chills/Shivering | 3 (1.3%) | 5 (2.2%)

In clinical trials, the following reported adverse events, assessed by investigators as treatment-related or causality unknown, occurred following oral or intravenous administration of ANZEMET in < 2% of adult patients receiving concomitant cancer chemotherapy:

Cardiovascular: Hypotension; edema, peripheral edema. The following events also occurred and with a similar frequency as placebo and/or active comparator: Mobitz I AV block, chest pain, orthostatic hypotension, myocardial ischemia, syncope, severe bradycardia, and palpitations. See PRECAUTIONS section for information on potential effects on ECG.

In addition, the following asymptomatic treatment-emergent ECG changes were seen at rates less than or equal to those for active or placebo controls: bradycardia, T-wave change, ST-T wave change, sinus arrhythmia, extrasystole (APCs or VPCs), poor R-wave progression, bundle branch block (left and right), nodal arrhythmia, U wave change, atrial flutter/fibrillation.

Furthermore, severe hypotension, bradycardia and syncope have been reported immediately or closely following IV administration.

Dermatologic: Rash, increased sweating.

Gastrointestinal System: Constipation, dyspepsia, abdominal pain, anorexia; pancreatitis.

Hearing, Taste and Vision: Taste perversion, abnormal vision, tinnitus, photophobia.

Hematologic: Hematuria, epistaxis, prothrombin time prolonged, PTT increased, anemia, purpura/hematoma, thrombocytopenia.

Hypersensitivity: Anaphylactic reaction, facial edema, urticaria.

Liver and Biliary System: Transient increases in AST (SGOT) and/or ALT (SGPT) values have been reported as adverse events in less than 1% of adult patients receiving ANZEMET in clinical trials. The increases did not appear to be related to dose or duration of therapy and were not associated with symptomatic hepatic disease. Similar increases were seen with patients receiving active comparator. Hyperbilirubinemia, increased GGT.

Metabolic and Nutritional: Alkaline phosphatase increased.

Musculoskeletal: Myalgia, arthralgia.

Nervous System: Flushing, vertigo, paresthesia, tremor; ataxia, twitching.

Psychiatric: Agitation, sleep disorder, depersonalization; confusion, anxiety, abnormal dreaming.

Respiratory System: Dyspnea, bronchospasm.

Urinary System: Dysuria, polyuria, acute renal failure.

Vascular (Extracardiac): Local pain or burning on IV administration; peripheral ischemia, thrombophlebitis/phlebitis.

Post-marketing Experience:

There are reports of wide complex tachycardia or ventricular tachycardia and of ventricular fibrillation cardiac arrest following intravenous administration.

To report SUSPECTED ADVERSE REACTIONS, contact Validus Pharmaceuticals LLC at 1-866-982-5438 or FDA at 1-800-FDA-1088 or www.fda.gov/medwatch.

OVERDOSAGE

There is no known specific antidote for dolasetron mesylate, and patients with suspected overdose should be managed with supportive therapy. Individual doses as large as 5 mg/kg intravenously or 400 mg orally have been safely given to healthy volunteers or cancer patients.

Following a suspected overdose of ANZEMET Injection, a patient found to have second-degree or higher AV conduction block with ECG should undergo cardiac telemetry monitoring.

It is not known if dolasetron mesylate is removed by hemodialysis or peritoneal dialysis.

Single intravenous doses of dolasetron mesylate at 160 mg/kg in male mice and 140 mg/kg in female mice and rats of both sexes (6.3 to 12.6 times the recommended human dose based on body surface area) were lethal. Symptoms of acute toxicity were tremors, depression and convulsions.

A 59-year-old man with metastatic melanoma and no known pre-existing cardiac conditions developed severe hypotension and dizziness 40 minutes after receiving a 15 minute intravenous infusion of 1000 mg (13 mg/kg) of dolasetron mesylate. Treatment for the overdose consisted of infusion of 500 mL of a plasma expander, dopamine, and atropine. The patient had normal sinus rhythm and prolongation of PR, QRS and QTc intervals on an ECG recorded 2 hours after the infusion. The patient’s blood pressure was normal 3 hours after the event and the ECG intervals returned to baseline on follow-up. The patient was released from the hospital 6 hours after the event.

DOSAGE AND ADMINISTRATION

The recommended doses of ANZEMET Tablets should not be exceeded.

Adults

The recommended oral dosage of ANZEMET (dolasetron mesylate) is 100 mg given within one hour before chemotherapy.

Pediatric Patients

The recommended oral dosage in pediatric patients 2 to 16 years of age is 1.8 mg/kg given within one hour before chemotherapy, up to a maximum of 100 mg. Safety and effectiveness in pediatric patients under 2 years of age have not been established.

In children for whom 100 mg is not appropriate based on their weight or ability to swallow tablets, the ANZEMET Injection solution may be mixed into apple or apple-grape juice for oral dosing in pediatric patients. The diluted product may be kept up to 2 hours at room temperature before use. However, ANZEMET Injection solution when administered intravenously is contraindicated in adult and pediatric patients for the prevention of nausea and vomiting associated with initial and repeat courses of emetogenic cancer chemotherapy due to dose dependent QT prolongation.

Use in the Elderly, Renal Failure Patients, or Hepatically Impaired Patients

No dosage adjustment is recommended, however; ECG monitoring is recommended for elderly and renally impaired patients (see WARNINGS and CLINICAL PHARMACOLOGY, Pharmacokinetics in Humans).

HOW SUPPLIED

ANZEMET® Tablets
(dolasetron mesylate, USP)
Strength | Quantity | NDC Number | Description
50 mg | 10 ct Bottle | 30698-220-10 | Light pink, film coated, round tablet debossed with “A” on one side and “50” on the other.

Store at 68° to 77°F (20° to 25°C) [See USP Controlled Room Temperature]. Protect from light.

PATIENT COUNSELING INFORMATION

Patients should be informed that ANZEMET may cause serious cardiac arrhythmias such as QT prolongation or heart block. Patients should be instructed to tell their health care provider right away if they perceive a change in their heart rate, if they feel lightheaded, or if they have a syncopal episode.

Patients should be informed that the chances of developing serious cardiac arrhythmias such as QT prolongation and Torsade de Pointes or heart block are higher in the following people:

- Patients with a personal or family history of abnormal heart rhythms, such as congenital long QT syndrome
- Patients with a personal history of sick sinus syndrome, atrial fibrillation with slow ventricular response or myocardial ischemia
- Patients who take medications that may prolong the PR interval, such as certain antihypertensives or medications that may prolong the QRS interval, such as antiarrythmic medications
- Patients who take medications, such as diuretics, which may cause electrolyte abnormalities
- Patients with hypokalemia or hypomagnesemia. Some types of chemotherapy cause hypokalemia and hypomagnesemia
- Elderly patients and renally impaired patients

ANZEMET should be avoided in these patients, since they may be more at risk for cardiac arrhythmias such as QT prolongation and Torsade de Pointes.

Advise patients of the possibility of serotonin syndrome with concomitant use of Anzemet and another serotonergic agent such as medications to treat depression and migraines. Advise patients to seek immediate medical attention if the following symptoms occur: changes in mental status, autonomic instability, neuromuscular symptoms with or without gastrointestinal symptoms.

Prescribing Information as of June 2021

Manufactured for and Distributed by:

Validus Pharmaceuticals LLC
Parsippany, NJ 07054
info@validuspharma.com
www.validuspharma.com
1-866-982-5438

Product of India

© 2021 Validus Pharmaceuticals LLC

60035-08 June 2021

PRINCIPAL DISPLAY PANEL

NDC 30698-220-10
Anzemet® Tablets
(dolasetron mesylate, USP)
50 mg
10 Tablets
Rx Only